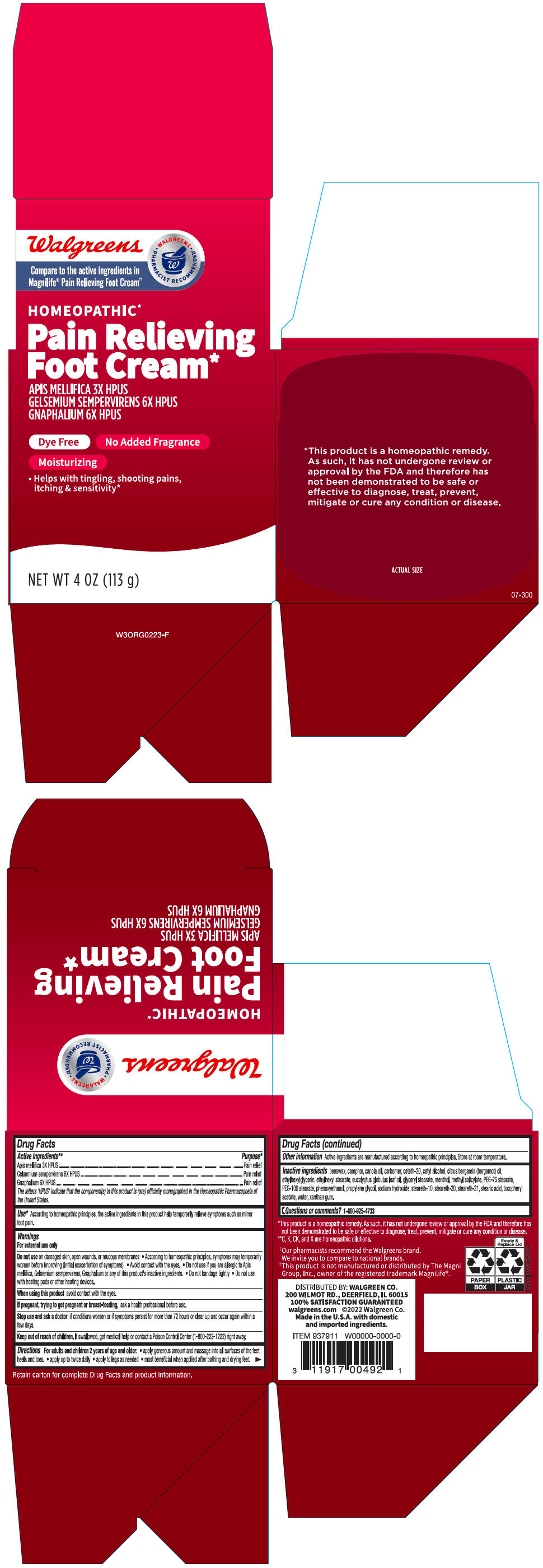 DRUG LABEL: Walgreens Pain Relieving Foot
NDC: 0363-9379 | Form: CREAM
Manufacturer: Walgreen Company
Category: homeopathic | Type: HUMAN OTC DRUG LABEL
Date: 20230227

ACTIVE INGREDIENTS: APIS MELLIFERA 3 [hp_X]/1 g; GELSEMIUM SEMPERVIRENS WHOLE 6 [hp_X]/1 g; PSEUDOGNAPHALIUM LUTEOALBUM LEAF 6 [hp_X]/1 g
INACTIVE INGREDIENTS: YELLOW WAX; CAMPHOR (SYNTHETIC); Canola Oil; CARBOMER HOMOPOLYMER, UNSPECIFIED TYPE; Ceteth-20; Cetyl Alcohol; BERGAMOT OIL; Ethylhexylglycerin; Ethylhexyl Stearate; EUCALYPTUS OIL; GLYCERYL MONOSTEARATE; MENTHOL, UNSPECIFIED FORM; Methyl Salicylate; PEG-75 Stearate; PEG-100 Stearate; Phenoxyethanol; Propylene Glycol; Sodium Hydroxide; Steareth-10; Steareth-20; Steareth-21; Stearic Acid; .ALPHA.-TOCOPHEROL ACETATE, DL-; Water; Xanthan Gum

Walgreens Pain Relieving Foot Cream
Pain Relief

Drug Facts

ACTIVE INGREDIENT

PURPOSE

Active ingredients [C, K, CK and X are homeopathic dilutions.] | Purpose
Apis mellifica 3X HPUS | Pain Relief
Gelsemium sempervirens 6X HPUS | Pain Relief
Gnaphalium 6X HPUS | Pain Relief

The letters 'HPUS' indicate that the component(s) in this product is (are) officially monographed in the Homeopathic Pharmacopeia of the United States.

Use [This product is a homeopathic remedy. As such, it has not undergone review or approval by the FDA and therefor has not been demonstrated to be safe or effective to diagnose, treat, prevent, mitigate or cure any condition or disease.]

According to homeopathic principles, the active ingredients in this product help temporarily relieve symptoms such as minor foot pain.

Warnings

For external use only

Do not use on damaged skin, open wounds, or mucous membranes

- According to homeopathic principles, symptoms may temporarily worsen before improving (Initial exacerbation of symptoms).
- Avoid contact with the eyes
- Do not use if you are allergic to Apis mellifica, Gelsenium sempervirens, Gmaphalium or any of this product's inactive ingredients.
- Do not bandage tightly
- Do not use with heating pads or other heating devices.

When using this product avoid contact with eyes.

PREGNANCY OR BREAST FEEDING

If pregnant, trying to get pregnant or breast-feeding, ask a health professional before use.

Stop use and ask a doctor if conditions worsen or if symptoms persist for more than 72 hours or clear up and occur again within a few days.

Keep out of reach of children. If swallowed, get medical help or contact a Poison Control Center (1-800-222-1222) right away.

DOSAGE AND ADMINISTRATION

Directions For Aduts and children 2 years of age and older:

- apply generous amount and massage into all surfaces of the feet, heels and toes.
- apply up to twice daily
- apply to legs as needed
- most beneficial when applied after bathing and drying feet.

Other information

Active ingredients are manufactured according to homeopathic principles. Store at room temperature.

Inactive ingredients

beeswax, camphor, canola oil, carbomer, ceteth-20, cetyl alcohol, citrus bergamia (bergamot) oil, ethylhexylglycerin, ethylhexyl stearate, eucalyptus globulus leaf oil, glyceryl stearate, menthol, methyl salicylate, PEG-75 stearate, PEG-100 stearate, phenoxyethanol, propylene glycol, sodium hydroxide, steareth-10, steareth-20, steareth-21, stearic acid, tocopheryl acetate, water, xanthan gum.

Questions or comments?

1-800-925-4733

DISTRIBUTED BY: WALGREEN CO.
200 WILMOT RD., DEERFIELD, IL 60015

PRINCIPAL DISPLAY PANEL - 113 g Jar Carton

Walgreens

Compare to the active ingredients in
Magnilife® Pain Relieving Foot Cream††

• WALGREENS •
PHARMACIST RECOMMENDED†

HOMEOPATHIC*

Pain Relieving
Foot Cream*

APIS MELLIFICA 3X HPUS
GELSEMIUM SEMPERVIRENS 6X HPUS
GNAPHALIUM 6X HPUS

Dye Free
No Added Fragrance
Moisturizing

- Helps with tingling, shooting pains,
  itching & sensitivity*

NET WT 4 OZ (113 g)